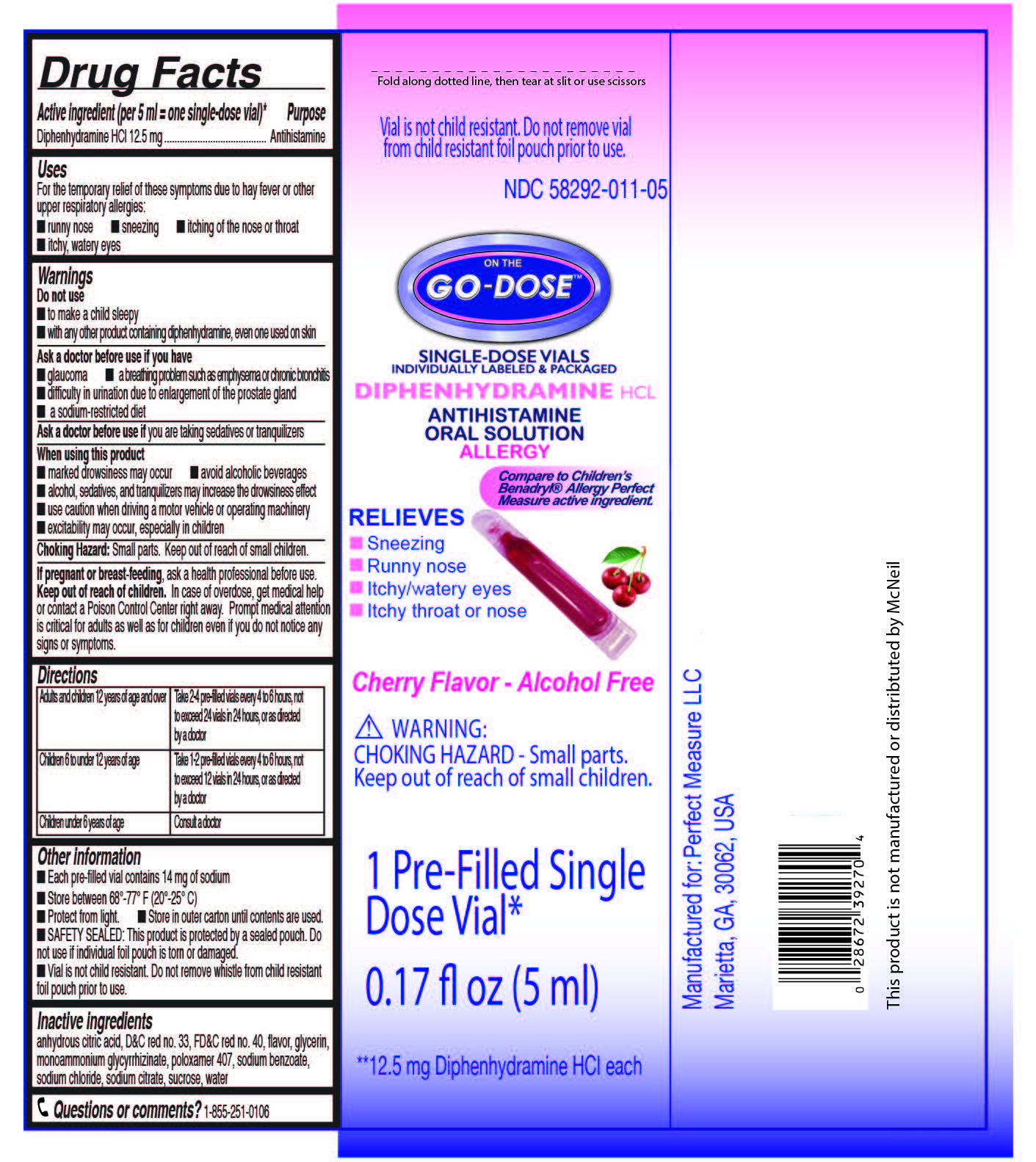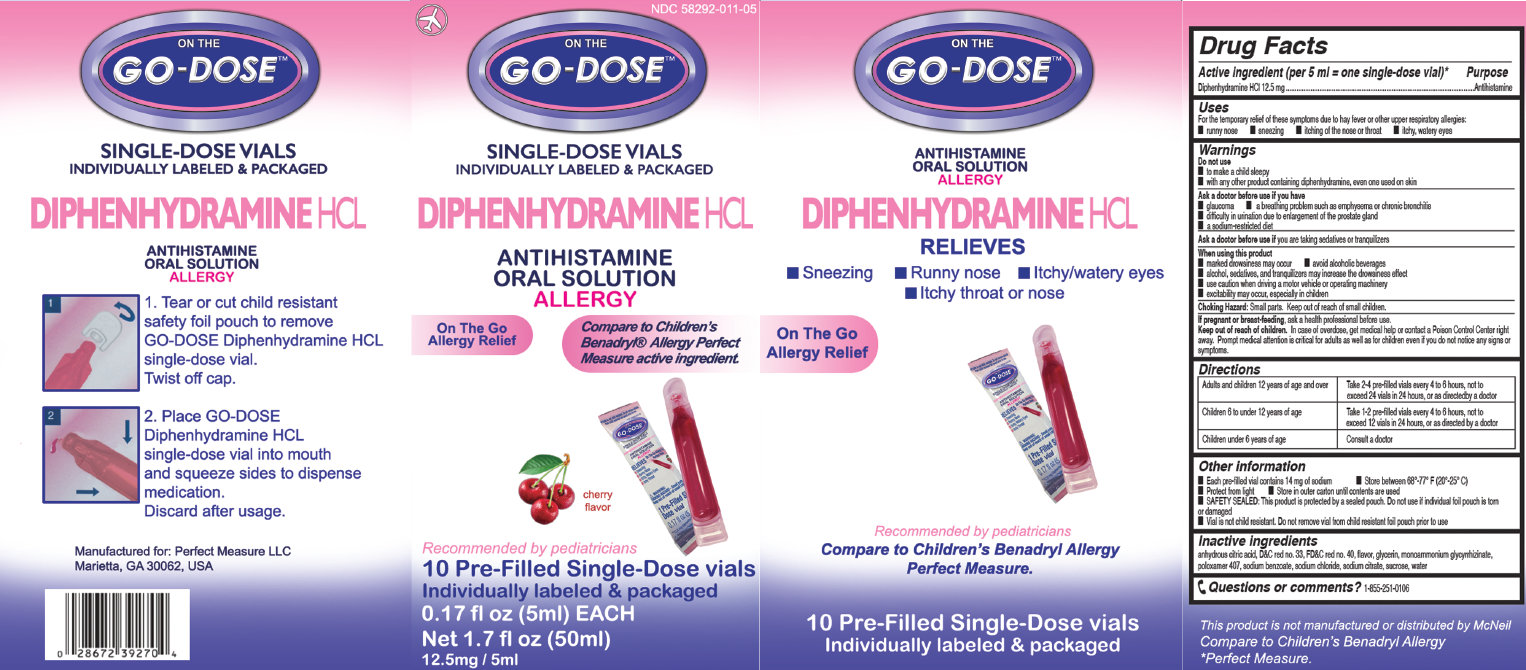 DRUG LABEL: On The GO-Dose
NDC: 58292-011 | Form: SOLUTION
Manufacturer: Perfect Measure LLC
Category: otc | Type: HUMAN OTC DRUG LABEL
Date: 20170131

ACTIVE INGREDIENTS: DIPHENHYDRAMINE HYDROCHLORIDE 12.5 mg/5 mL
INACTIVE INGREDIENTS: ANHYDROUS CITRIC ACID; D&C RED NO. 33; FD&C RED NO. 40; GLYCERIN; AMMONIUM GLYCYRRHIZATE; POLOXAMER 407; SODIUM BENZOATE; SODIUM CHLORIDE; SODIUM CITRATE; SUCROSE; WATER

On The GO-Dose Diphenhydramine HCL Anti-Histamine Oral Solution

Active ingredient (per 5 ml = one pre-filled vial)

Diphenhydramine HCl 12.5 mg

Purpose

Antihistamine

Uses

For the temporary relief of these symptoms due to hay fever or other upper respiratory allergies:

- runny nose
- sneezing
- itching of the nose or throat
- itchy, watery eyes

Warnings

Do not use

- to make a child sleepy
- with any other product containing diphenhydramine, even one used on skin

Ask a doctor before use if you have

- glaucoma
- difficulty in urination due to enlargement of the prostate gland
- a sodium-restricted diet
- a breathing problem such as emphysema or chronic bronchitis

Ask a doctor or pharmacist before use if you

are taking sedatives or tranquilizers

When using this product

marked drowsiness may occur

avoid alcoholic beverages

alcohol, sedatives, and tranquilizers may increase the drowsiness effect

use caution when driving a motor vehicle or operating machinery

excitability may occur, especially in children

If pregnant or breast-feeding,

ask a health professional before use.

Keep out of reach of children.

In case of overdose, get medical help or contact a Poison Control Center right away. Prompt medical attention is critical for adults as well as for children even if you do not notice any signs or symptoms.

Directions

Adults and children 12 years of age and over | Take 2-4 pre-filled vial every 4 to 6 hours, not to exceed 24 whistles in 24 hours, or as directed by a doctor
Children 6 to under 12 years of age | Take 1-2 pre-filled vial every 4 to 6 hours, not to exceed 12 whistles in 24 hours, or as directed by a doctor
Children under 6 years of age | Consult a doctor

Other information

- Each pre-filled vial contains 14 mg of sodium
- Protect from light.
- SAFETY SEALED: This product is protected by a sealed pouch. Do not use if individual foil pouch is torn or damaged.
- Whistle is not child resistant. Do not remove whistle from child resistant foil pouch prior to use.
- Store between 68 degrees-77 degrees F (20 degrees - 25 degrees C)
- Store in outer carton until contents are used.

Inactive ingredients

anhydrous citric acid, DandC red no. 33, FDandC red no.40, flavor, glycerin, monoammonium glycyrrhizinate, poloxamer 407, sodium benzoate, sodium chloride, sodium citrate, sucrose, water

Questions or comments?

1-855-251-0106